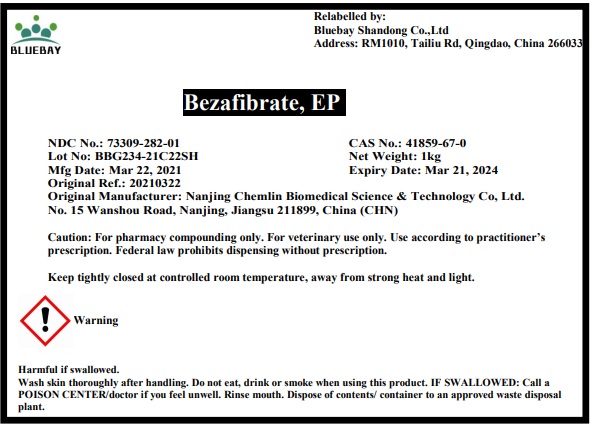 DRUG LABEL: Bezafibrate
NDC: 73309-282 | Form: POWDER
Manufacturer: BLUEBAY SHANDONG CO.,LTD
Category: other | Type: BULK INGREDIENT
Date: 20210513

ACTIVE INGREDIENTS: BEZAFIBRATE 1 kg/1 kg

Bezafibrate